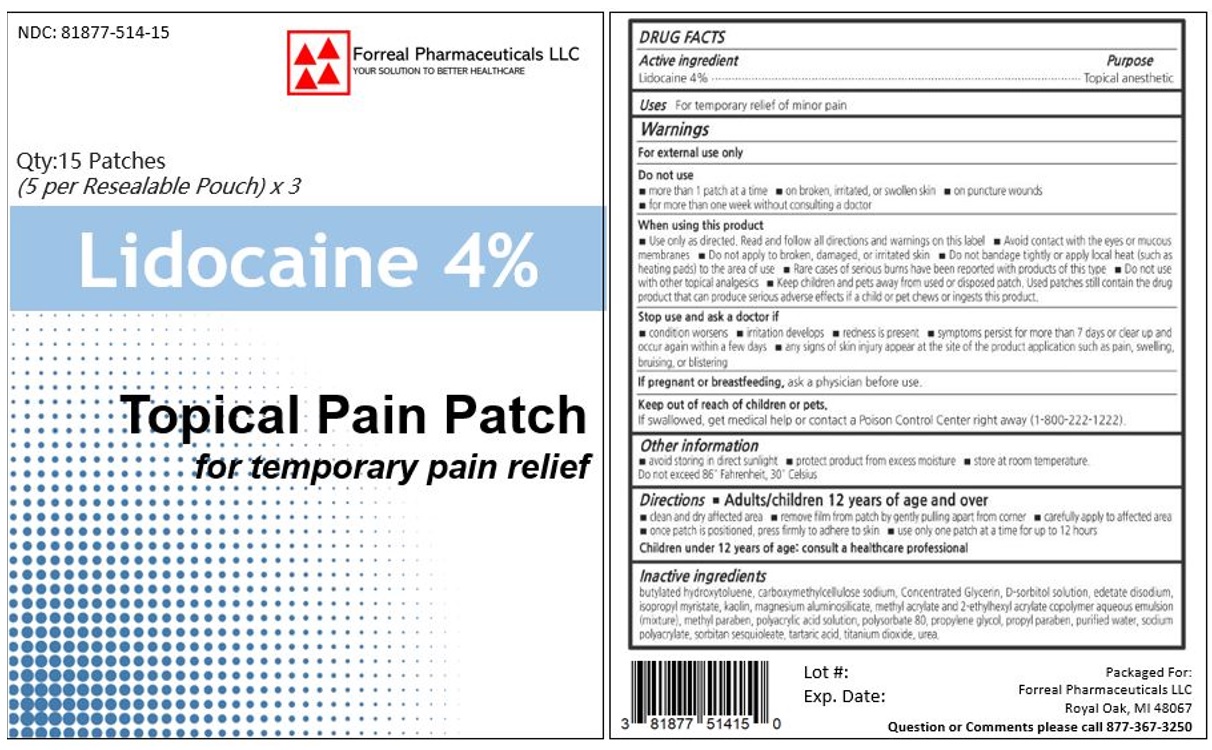 DRUG LABEL: Lidocaine
NDC: 81877-514 | Form: PATCH
Manufacturer: FORREAL PHARMACEUTICALS LLC
Category: otc | Type: HUMAN OTC DRUG LABEL
Date: 20240606

ACTIVE INGREDIENTS: LIDOCAINE 40 mg/1 g
INACTIVE INGREDIENTS: BUTYLATED HYDROXYTOLUENE; CARBOXYMETHYLCELLULOSE SODIUM; GLYCERIN; SORBITOL; EDETATE DISODIUM; ISOPROPYL MYRISTATE; KAOLIN; SILODRATE ANHYDROUS; 2-ETHYLHEXYL ACRYLATE; METHYLPARABEN; POLYACRYLIC ACID (250000 MW); POLYSORBATE 80; PROPYLENE GLYCOL; PROPYLPARABEN; WATER; SODIUM POLYACRYLATE (2500000 MW); SORBITAN SESQUIOLEATE; TARTARIC ACID; TITANIUM DIOXIDE; UREA

Lidocaine 4%

ACTIVE INGREDIENT

Lidocaine 4%

PURPOSE

Topical Anesthetic

INDICATIONS AND USAGE

For the temporary relief of pain

WARNINGS

For external use only

Do not use

- More than 1 pathch at a time
- On wounds or damaged skin
- With a heating pad
- If you are allergic to any ingredients of this product

When using this product

- Use only as directed
- Avoid contact with the eyes, mucous membranes or rashes
- Do not bandage tightly

Stop use and ask a doctor if

- Localized skin reactions occur, such as rash, itching, redness, irritation, pain, swelling and blistering
- Conditions worsen
- Symptoms persist for more than 7 days
- Symptoms clear up and occur again within a few days

If pregnant or breast-feeding

Ask a health professional before use.

Keep out of reach of children

If swallowed, get medical help or contact a Poison Control Center right away.

Directions

Adults and children 12 years of age and over:

- Clean and dry the affected area
- Open pouch and remove one patch
- Apply 1 patch at a time to affected area; not more than 3 to 4 times daily
- Reseal pouch containing unused patches after each use
- Remove patch from the skin after at most 8-hour application

Children under 12 years of age: Consult a doctor

Other information:

- Avoid storing product in direct sunlight
- Protect product from excessive moisture

INACTIVE INGREDIENT

Other ingredients: Acrylic Adhesive, Flaxseed oil, and Polysorbate 80

Questions or comments? 877-367-3250

PACKAGE LABEL

Packaged For:

Forreal Pharmaceuticals LLC

Royal Oak, MI 48067

Questions or Comments please call 877-367-3250

NDC 81877-514-15

Qty:15 Patches

(5 per Resealable Pouch) x 3

Lidocaine 4%

Topical Pain Patch

for temporary pain relief